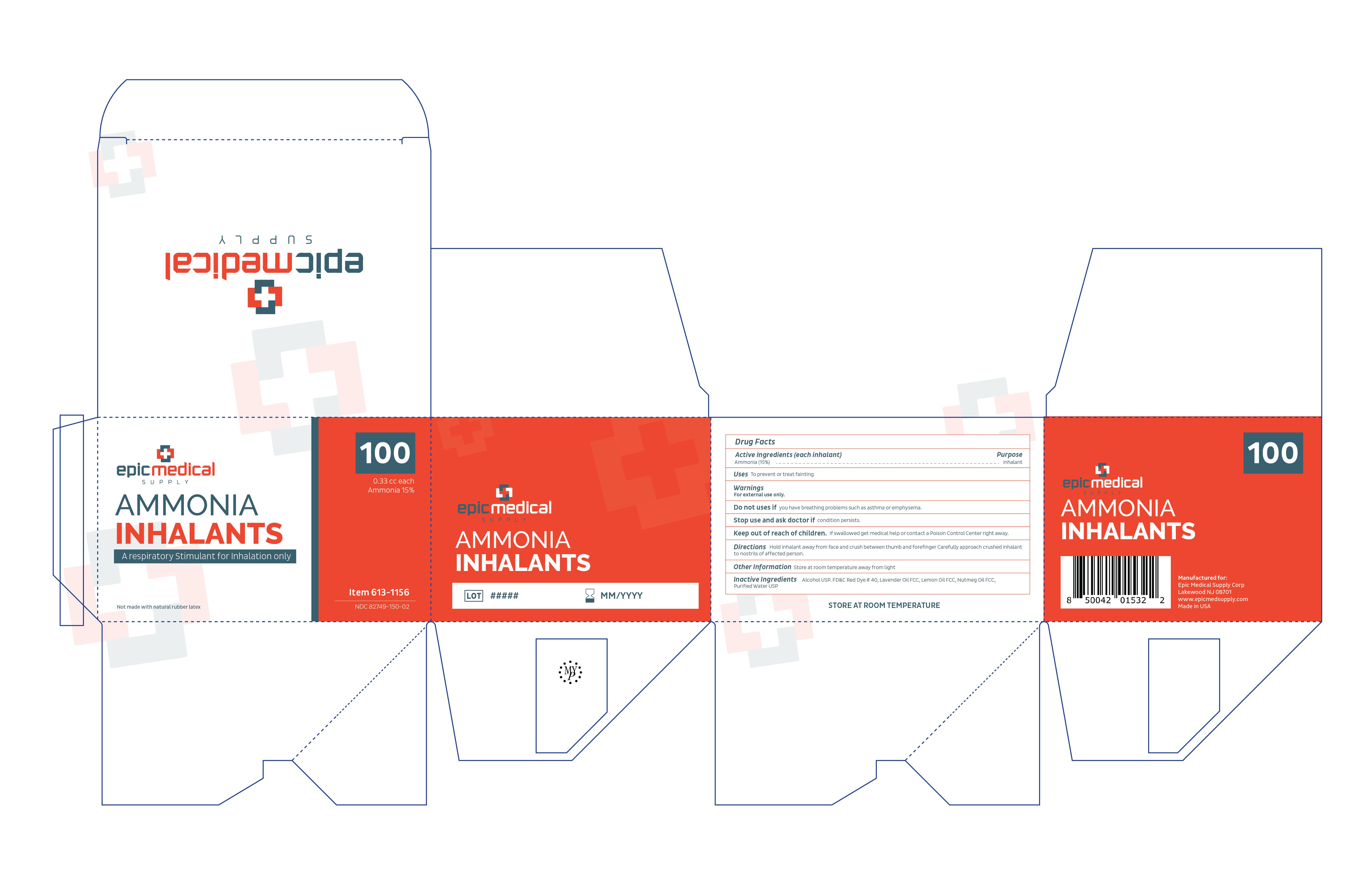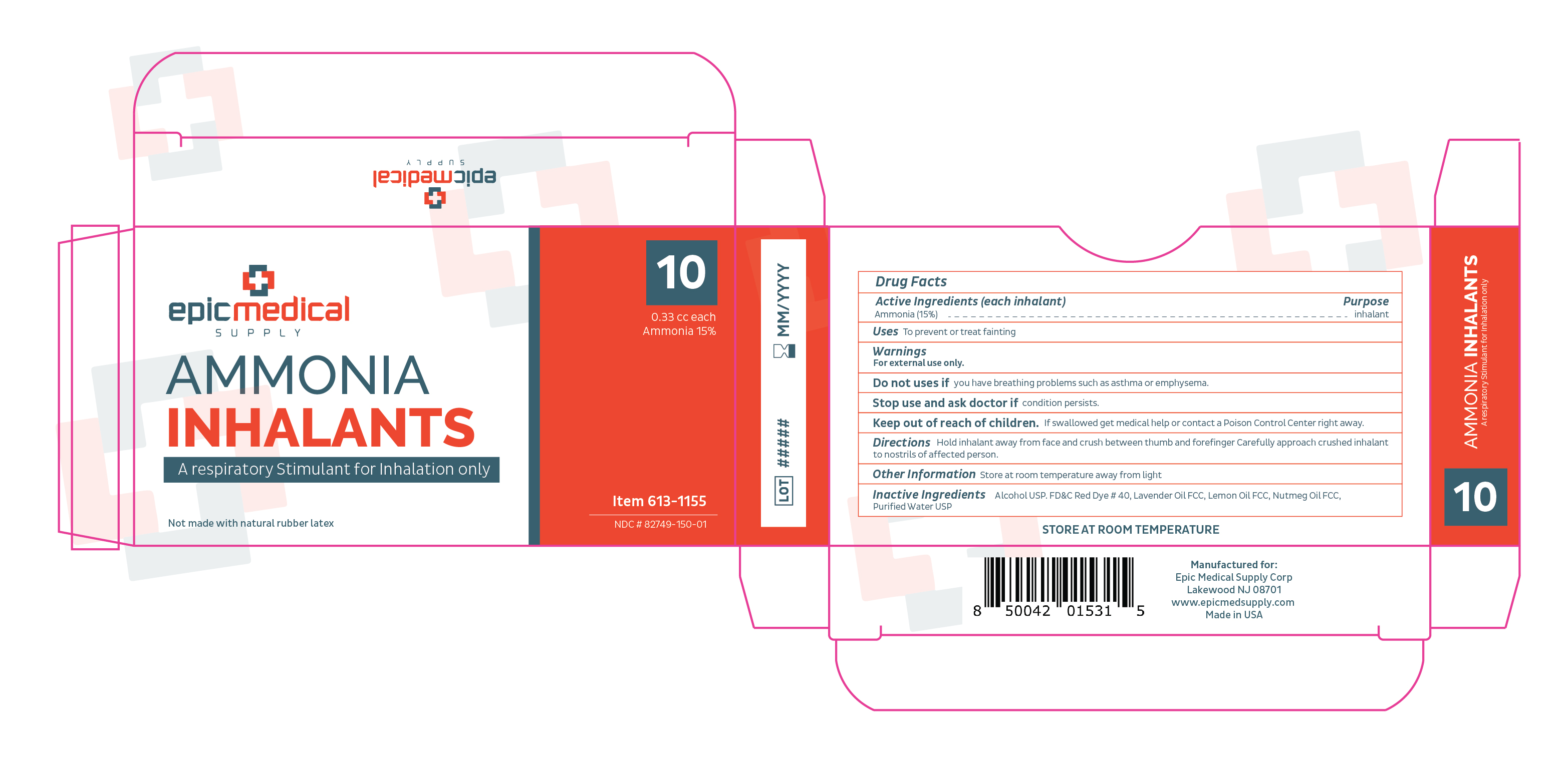 DRUG LABEL: ammonia inhalants
NDC: 82749-150 | Form: INHALANT
Manufacturer: Epic Medical Supply Corp
Category: otc | Type: HUMAN OTC DRUG LABEL
Date: 20240903

ACTIVE INGREDIENTS: AMMONIA 0.045 g/0.3 mL
INACTIVE INGREDIENTS: ALCOHOL; FD&C RED NO. 40; WATER

ammonia inhalants

Active Ingredients (each inhalant)

Ammonia (15%)

Purpose

inhalant

Uses

To prevent or treat fainting.

Warnings

For external use only.

Do not use if you have breathing problems such as asthma or emphysema.

Stop use and ask a doctor if condition persists.

Keep out of reach of children. If swallowed get medical help or contact a Poison Control Center right away.

Directions

Hold inhalant away from face and crush between thumb and forefinger. Carefully approach crushed inhalant to nostrils of affected person.

Other Information

Store at room temperature away from light.

Inactive Ingredients

Alcohol USP, FD&C Red Dye # 40, Lavender Oil FCC, Lemon Oil FCC, Nutmeg Oil FCC, Purified Water USP.